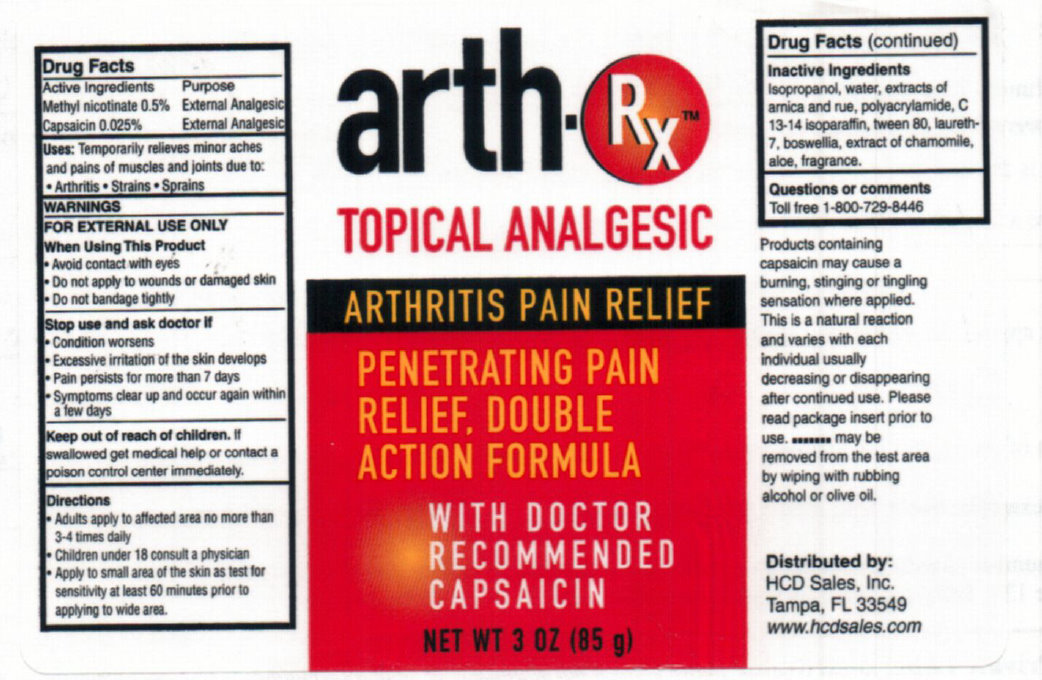 DRUG LABEL: Arth RX Topical Analgesic
NDC: 76069-100 | Form: LOTION
Manufacturer: HCD Sales
Category: otc | Type: HUMAN OTC DRUG LABEL
Date: 20231106

ACTIVE INGREDIENTS: METHYL NICOTINATE 0.5 g/100 g; CAPSAICIN 0.025 g/100 g
INACTIVE INGREDIENTS: ISOPROPYL ALCOHOL; WATER; POLYQUATERNIUM-7 (70/30 ACRYLAMIDE/DADMAC; 1600 KD); C13-14 ISOPARAFFIN; POLYSORBATE 80; LAURETH-7; ALOE

Arth RX Topical Analgesic

ACTIVE INGREDIENT

Active Ingredients Purpose Methyl nicotinate 0.5% External Analgesic Capsaicin 0.025 % External Analgesic

PURPOSE

Uses: Temporarily relieves minor aches and pains of muscles and joints due to:

- Arthritis - Strains - Sprains

WARNINGS

FOR EXTERNAL USE ONLY

When Using This Product

- Avoid contact with eyes - Do not apply to wounds or damaged skin - Do not bandage tightly

Stop use and ask doctor if

- Condition worsens - Excessive irritation of the skin develops - Pain persists for more than 7 days - Symptoms clear up and occur again within a few days

Keep out of reach of children. If swallowed get medical help or contact a poison control center immediately.

DOSAGE AND ADMINISTRATION

Directions - Adults apply to affected area no more than 3-4 times daily - Children under 18 consult a physician - Apply to small area of the skin as test for sensitivity at least 60 minutes prior to applying to wide area.

Inactive Ingredients

Isopropanol, water, extracts of arnica and rue, polyacrylamide, C 13-14 isoparaffin. tween 80, laureth-7, boswellia, extract of chamomile, aloe, fragrance.

Questions or comments

Toll free 1-800-729-8446

DESCRIPTION

Products containing capsaicin may cause a burning, stinging or tingling sensation where applied. This is a natural reaction and varies with each individual usually decreasing or disappearing after continued use. Please read package insert prior to use. .......... may be removed from the test area by wiping or olive oil.

Distributed by: HCD sales, Inc, Tampa, FL 33549 www.hcdsales.com

PACKAGE LABEL

arth.Rx TOPICAL ANALGESIC ARTHRITIS PAIN RELIEF PENETRATING PAIN RELIEF, DOUBLE ACTION FORMULA WITH DOCTOR RECOMMENDED CAPSAICIN NEW WT 3 OZ (85 g)